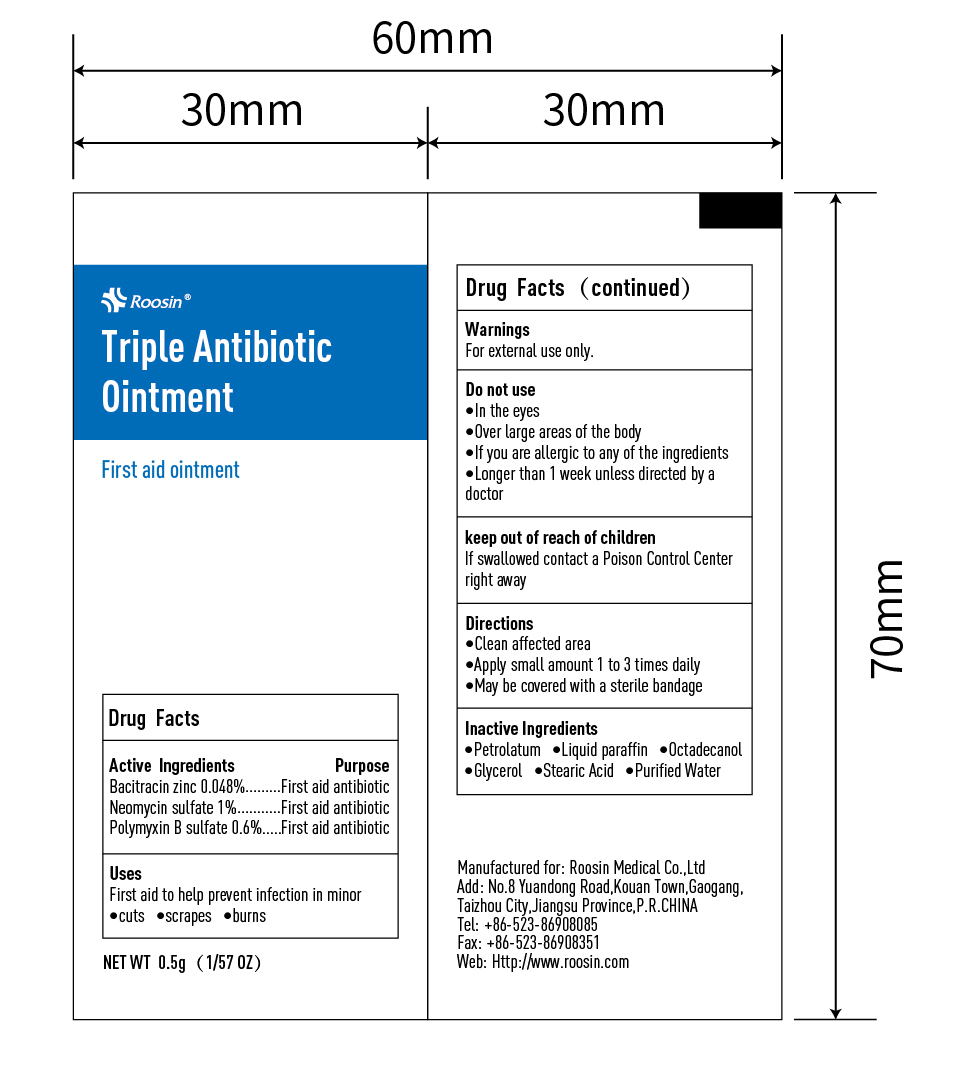 DRUG LABEL: Roosin Triple Antibiotic
NDC: 81552-005 | Form: OINTMENT
Manufacturer: ROOSIN MEDICAL CO., LTD
Category: otc | Type: HUMAN OTC DRUG LABEL
Date: 20210424

ACTIVE INGREDIENTS: BACITRACIN ZINC 0.048 g/100 g; NEOMYCIN SULFATE 1 g/100 g; POLYMYXIN B SULFATE 0.6 g/100 g
INACTIVE INGREDIENTS: PETROLATUM; PARAFFIN; OCTADECANOL (MIXTURE OF ISOMERS); WATER; STEARIC ACID; GLYCEROL FORMAL

81552-004 Triple Antibiotic Ointment

Active Ingredient

Bacitracin Zinc 0.048%

Neomycin Sulfate 1%

Polymyxin B Sulfate 0.6%

Purpose

First aid antibiotic

First aid antibiotic

First aid antibiotic

Use

First aid to help prevent infection in minor cuts scrapes burns

WARNINGS

For external use only

Do not use

- In the eyes
- Over large areas of the body
- If you are allergic to any of the ingredients
- Longer than 1 week unless directed by a doctor

Keep out of reach of children. If swallowed, get medical help or contact a poison control center right away

Directions

Clean affected area

Apply small amount 1 to 3 times daily

May be covered with a sterile bandage

Inactive ingredients

Petrolactum, Liquid Paraffin, Octadecanol, Glycerol, Stearic Acid, Purified Water